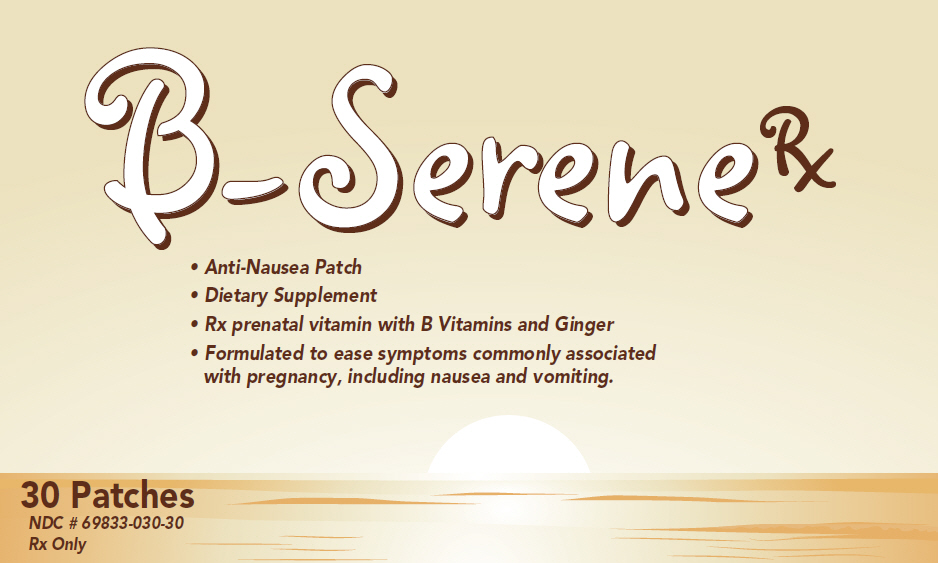 DRUG LABEL: B-Serene Rx
NDC: 69833-030 | Form: PATCH
Manufacturer: Spring Hill Therapeutics LLC
Category: other | Type: DIETARY SUPPLEMENT
Date: 20160114

ACTIVE INGREDIENTS: Pyridoxine Hydrochloride 75 mg/1 1; Cyanocobalamin 12 ug/1 1; Folic Acid 1200 ug/1 1; Ginger 500 mg/1 1
INACTIVE INGREDIENTS: 2-Ethylhexyl Acrylate; Methacrylic Acid; Bentonite; Sodium Stearate

B-SereneRx

STATEMENT OF IDENTITY

Supplement Facts
Active Ingredients Serving Size: 1 patch | Amount per serving | %DV
Vitamin B6 (Pyridoxine Hydrochloride) | 75 mg | 3000%
Vitamin B12 (Cyanocobalamin) | 12 mcg | 150%
Folic Acid | 1.2 mg | 150%
Ginger | 500 mg | [Daily Value (DV) not established]
Daily Value for adults and children four or more years of age

Uses

B-Serene Rx is indicated to provide B-Vitamin supplementation, with ginger to help calm preganancy related nausea and vomiting (morning sickness), and may be used in conjunction with a physician prescribed prenatal regimen.

Warnings

For external use only • Use only as directed • Avoid contact with eyes and mucous membranes • Do not use with heating devices or pads • Do not bandage tightly • If contact does occur with eyes rinse with cold water and call a doctor • Folic acid alone is improper therapy in the treatment of pernicious anemia and other megaloblastic anemias where vitamin B12 is deficient. Folic acid in doses above 0.1 mg daily may obscure pernicious anemia in that hematologic remission can occur while neurological manifestations progress. While prescribing this nutritional supplement for pregnant women, nursing mothers or for women prior to conception, their medical condition and any drugs, herbs and/or supplements consumption should be considered. • Keep this product out of reach of children. In case of accidental overdose, call a doctor or poison control center immediately. Concomitant use of ginger in pateints with heavy bleeding disorders, or who are on anti-coagulant or anti-platelet therapy, may increase the risk of bleeding.

Inactive Ingredients

Methacrylic acid, ethylhexylacrylate, bentonite, sodium stearate.

Do not use

On wounds or damaged skin. Children under 12 years old, consult a doctor. If you are allergic to any ingredients in this product. If condition worsens, or if symptoms persist for more than 7 days or clear up and occur again within a few days, discontinue use of this product and consult a doctor.

Keep out of the reach of children.

Directions

Use one patch as directed or every 6-12 hours.

Other Information

Store at 25°C (77°F) excursions permitted to 15°-30°C (59°-86° F)

See USP Controlled Room Temperature • Protect from freezing.

HEALTH CLAIM

These statements have not been approved by the FDA, This product is not intended to diagnose, treat, cure or prevent any disease.

SPRING HILL
THERAPEUTICS

8270 Woodland Center Blvd. • Tampa, FL 33614
FOR QUESTIONS CALL 813-388-8735

PRINCIPAL DISPLAY PANEL - 30 Patch Bag Label

B-SereneRx

- Anti-Nausea Patch
- Dietary Supplement
- Rx prenatal vitamin with B Vitamins and Ginger
- Formulated to ease symptoms commonly associated
  with pregnancy, including nausea and vomiting.

30 Patches
NDC # 69833-030-30
Rx Only